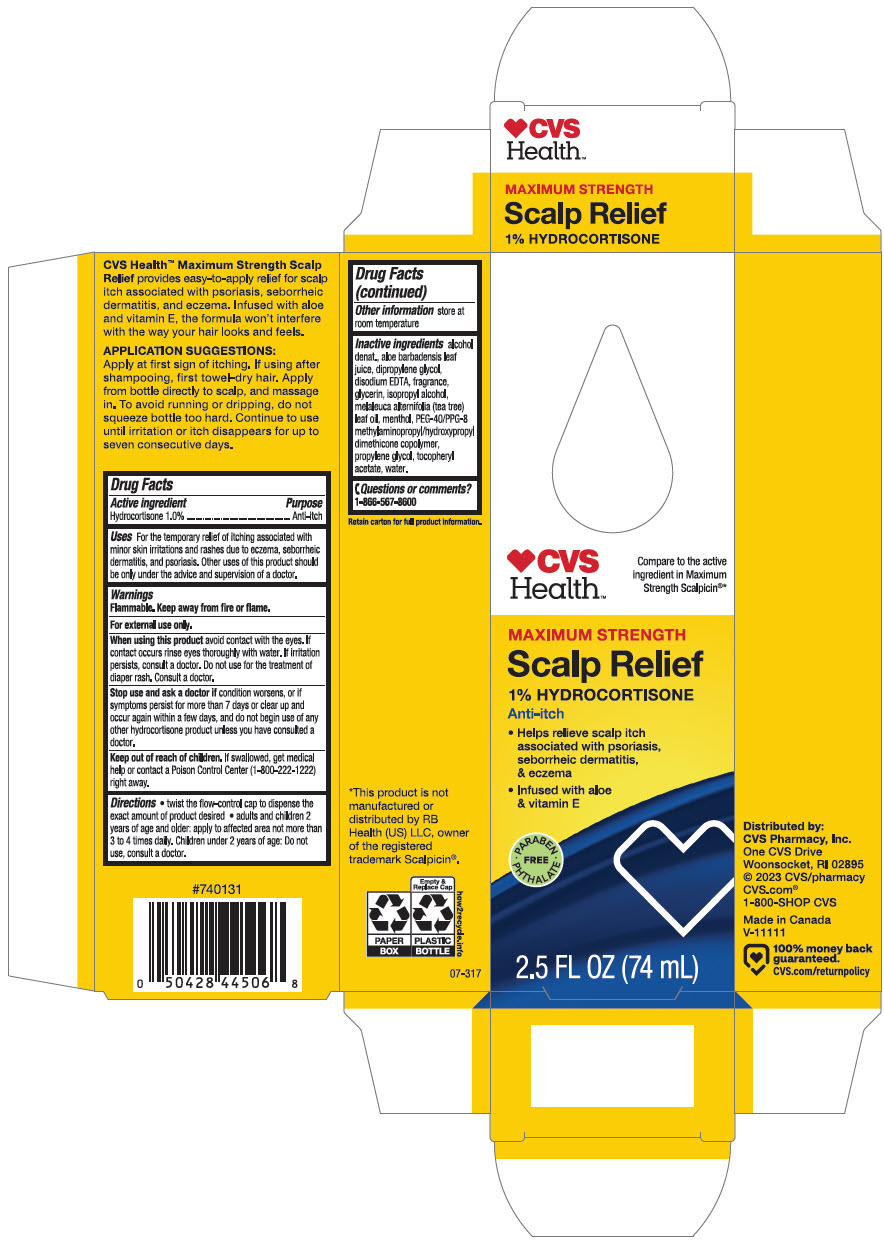 DRUG LABEL: CVS Health Maximum Strength Scalp Relief
NDC: 51316-068 | Form: LIQUID
Manufacturer: CVS Health
Category: otc | Type: HUMAN OTC DRUG LABEL
Date: 20240819

ACTIVE INGREDIENTS: HYDROCORTISONE 10 mg/1 mL
INACTIVE INGREDIENTS: ALCOHOL; ALOE VERA LEAF; Dipropylene Glycol; EDETATE DISODIUM; Glycerin; Isopropyl Alcohol; TEA TREE OIL; MENTHOL, UNSPECIFIED FORM; Propylene Glycol; .ALPHA.-TOCOPHEROL ACETATE, DL-; Water

CVS Health™ Maximum Strength Scalp Relief
Anti-itch

Drug Facts

Active ingredient

Hydrocortisone 1.0%

Purpose

Anti-itch

Uses

For the temporary relief of itching associated with minor skin irritations and rashes due to eczema, seborrheic dermatitis, and psoriasis. Other uses of this product should be only under the advice and supervision of a doctor.

Warnings

Flammable. Keep away from fire or flame.

For external use only.

When using this product avoid contact with the eyes. If contact occurs rinse eyes thoroughly with water. If irritation persists, consult a doctor. Do not use for the treatment of diaper rash. Consult a doctor.

Stop use and consult a doctor if

- condition worsens, or if symptoms persist for more than 7 days or clear up and occur again within a few days, and do not begin use of any other hydrocortisone product unless you have consulted a doctor.

Keep out of reach of children. If swallowed, get medical help or contact a Poison Control Center (1-800-222-1222) right away.

Directions

- twist the flow-control cap to dispense the exact amount of product desired
- adults and children 2 years of age and older: apply to affected area not more than 3 to 4 times daily. Children under 2 years of age: Do not use, consult a doctor.

Other information

store at room temperature

Inactive ingredients

alcohol denat., aloe barbadensis leaf juice, dipropylene glycol, disodium EDTA, fragrance, glycerin, isopropyl alcohol, melaleuca alternifolia (tea tree) leaf oil, menthol, PEG-40/PPG-8 methylaminopropyl/hydroxypropyl dimethicone copolymer, propylene glycol, tocopheryl acetate, water.

Questions or comments?

1-866-567-8600

Distributed by:
CVS Pharmacy, Inc.
One CVS Drive
Woonsocket, RI 02895

PRINCIPAL DISPLAY PANEL - 74 mL Bottle Carton

CVS
Health™

Compare to the active
ingredient in Maximum
Strength Scalpicin®*

MAXIMUM STRENGTH
Scalp Relief
1% HYDROCORTISONE
Anti-itch

- Helps relieve scalp itch
  associated with psoriasis,
  seborrheic dermatitis,
  & eczema
- Infused with aloe
  & vitamin E

• PARABEN
PHTHALATE •
FREE

2.5 FL OZ (74 mL)